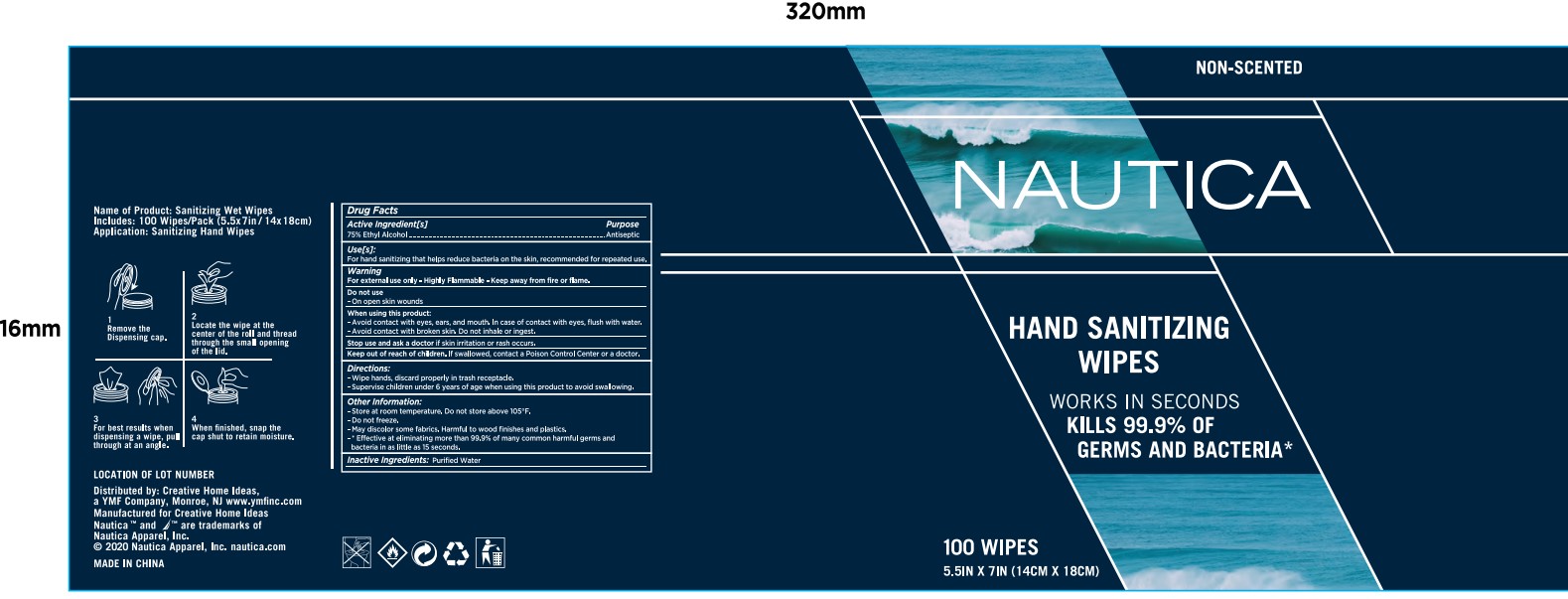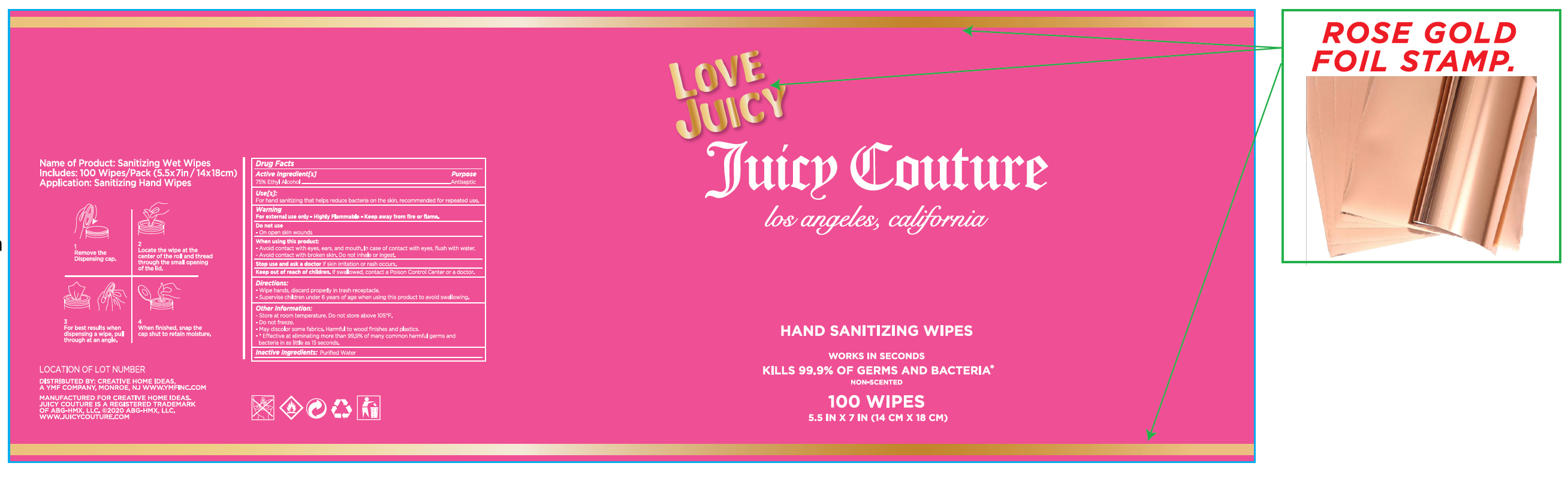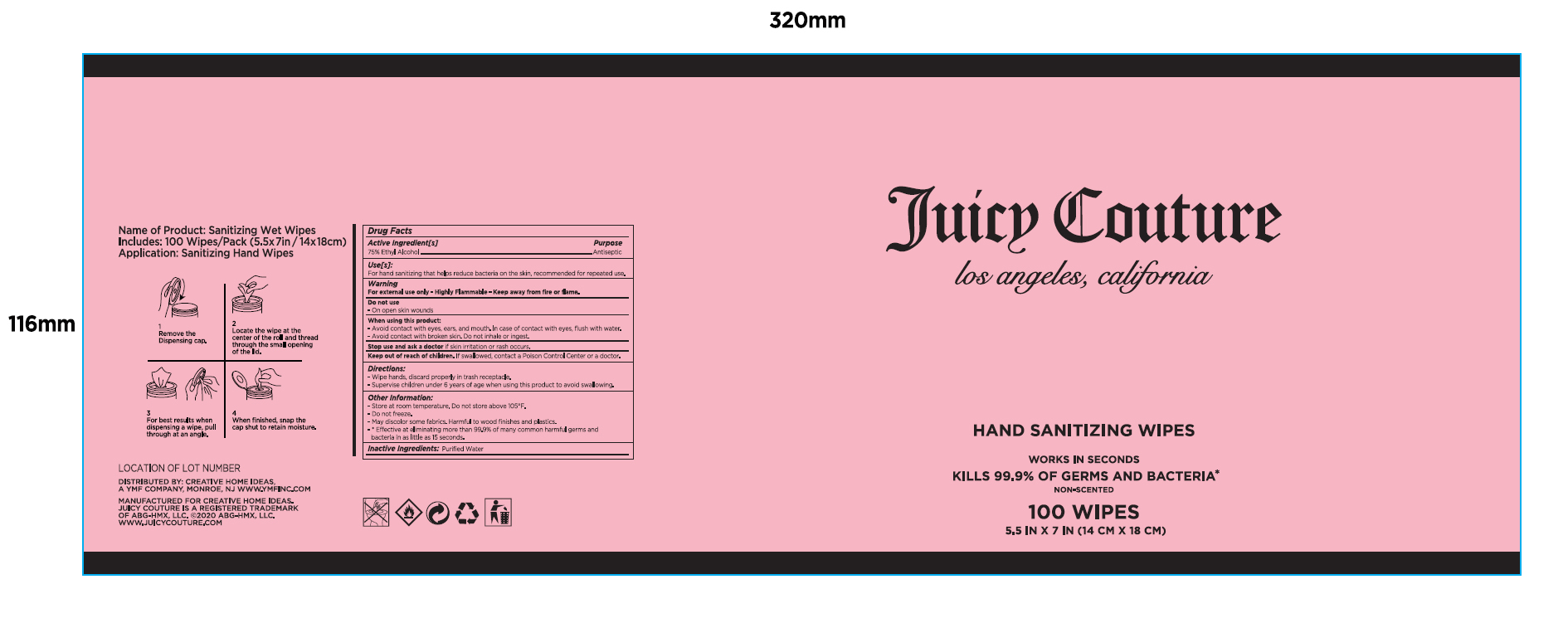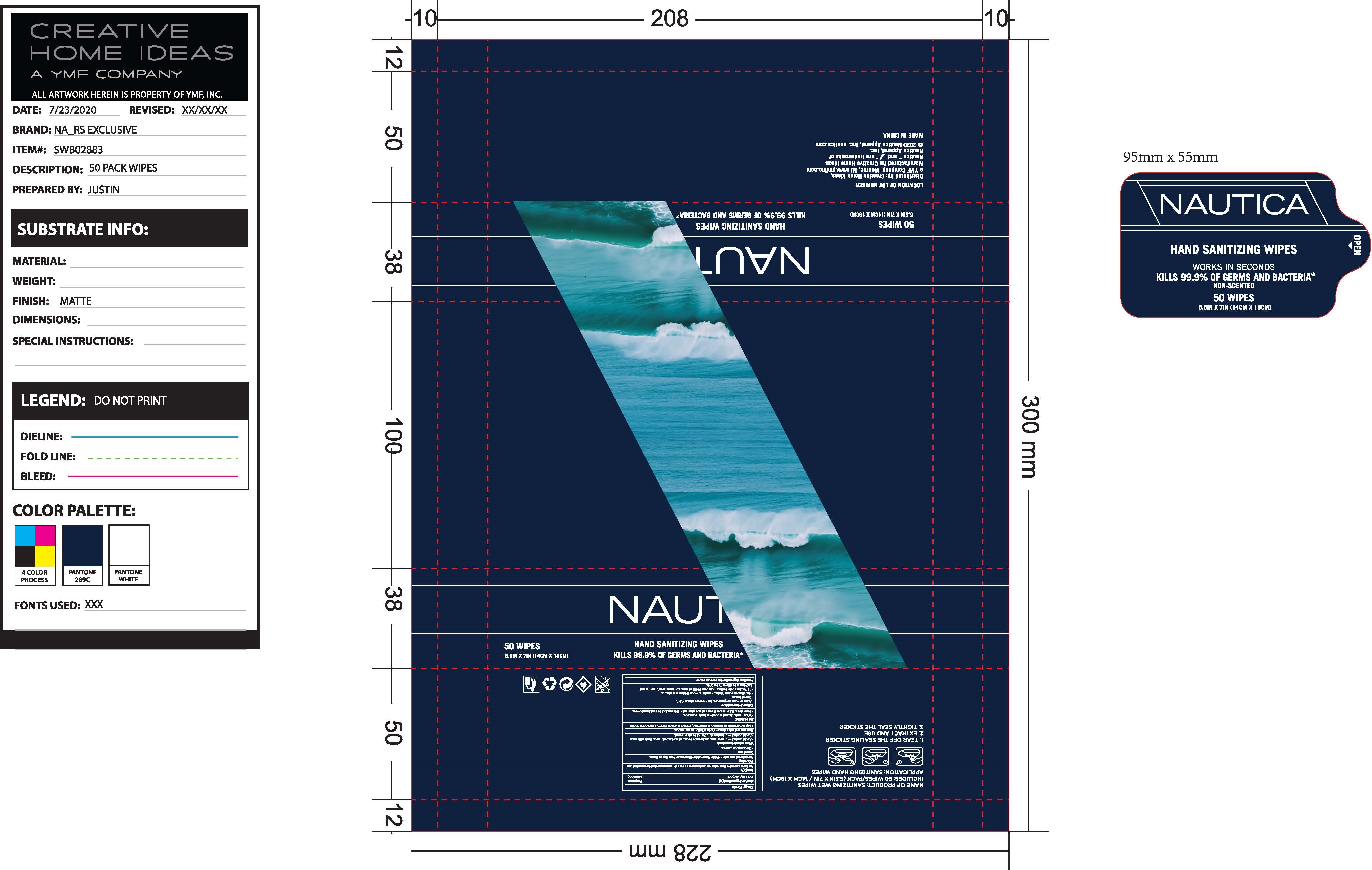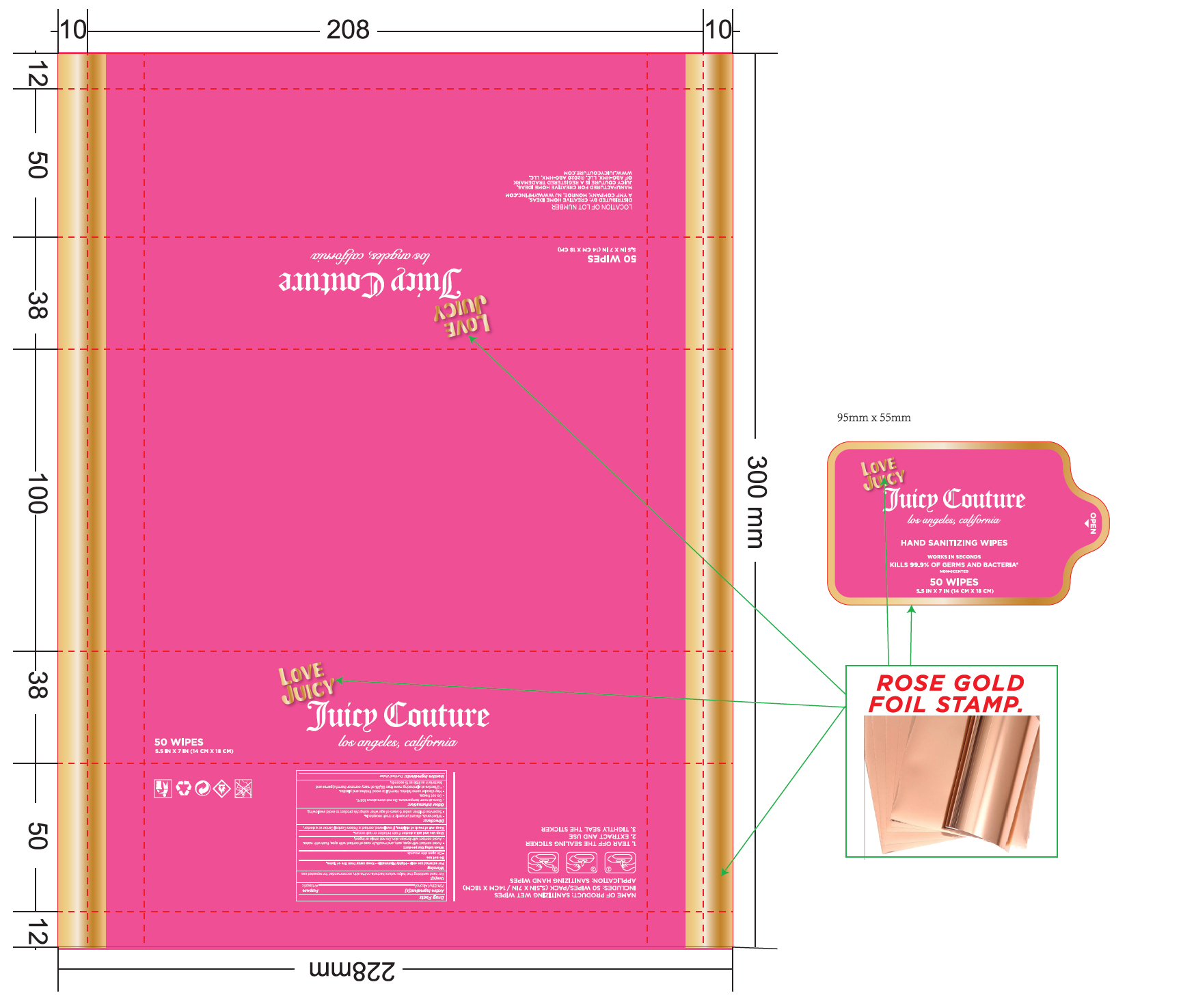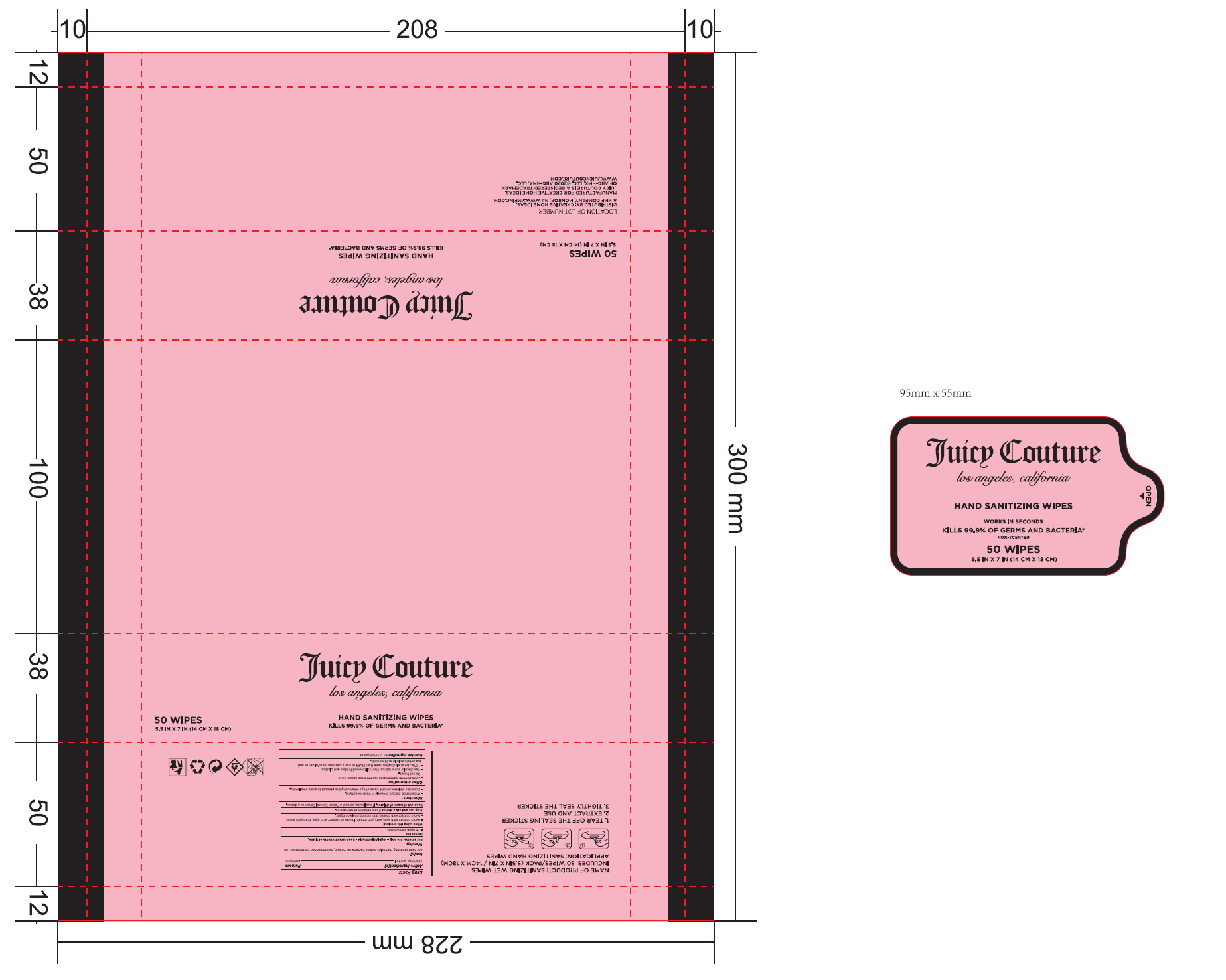 DRUG LABEL: sanitizing wipes
NDC: 78198-012 | Form: CLOTH
Manufacturer: Y M F Carpets, Inc.
Category: otc | Type: HUMAN OTC DRUG LABEL
Date: 20200813

ACTIVE INGREDIENTS: ALCOHOL 0.75 mL/1 g
INACTIVE INGREDIENTS: WATER

sanitizing wipes

ACTIVE INGREDIENT

75% Ethyl Alcohol. Purpose: Antiseptic

PURPOSE

Antiseptic

Use[s]

For hand sanitizing that helps reduce bacteria on the skin, recommended for repeated use.

Warnings

For external use only-Highly Flammable - Keep away from fire or flame

Do not use

- On open skin wounds

When using this product

- Avoid contact with eyes, ears, and mouth. In case of contact with eyes, flush with water.

- Avoid contact with broken skin. Do not inhale or ingest.

Stop use and ask a doctor

if skin irritation or rash occurs.

Keep out of reach of children

If swallowed, contact a Poison Control Center or a doctor

Directions

-Wipe hands, discard properly in trash receptacle.

-Supervise children under 6 years of age when using this product to avoid swallowing.

Other information

- Store at room temperature. Do not store above 105F

- Do not freeze.

- May discolor some fabrics. Harmful to wood finishes and plastics.

-*Effective at eliminating more than 99.9% of many common harmful germs and baceria in as little as 15 seconds.

Inactive Ingredients

Purified Water

Package Label - Principal Display Panel

100 PCS NDC: 78198-012-01

NON-SCENTED

NAUTICA

HAND SANITIZING

WIPES

WORKS IN SECONDS

KILLS 99.9% OF GERMS AND BACTERIA*

100 WIPES

5.5IN X 7IN (14CM X 18CM)

100 PCS NDC: 78198-012-02

LOVE

JUICY

JUICY COUTURE

los angeles, california

HAND SANITIZING WIPES

WORKS IN SECONDS

KILLS 99.9% OF GERMS AND BACTERIA*

NON-SCENTED

100 WIPES

5.5IN X 7IN (14CM X 18CM)

100 PCS NDC: 78198-012-03

JUICY COUTURE

los angeles, california

HAND SANITIZING WIPES

WORKS IN SECONDS

KILLS 99.9% OF GERMS AND BACTERIA*

NON-SCENTED

100 WIPES

5.5IN X 7IN (14CM X 18CM)

50 PCS NDC: 78198-012-04

NAUTICA

HAND SANITIZING WIPES

WORKS IN SECONDS

KILLS 99.9% OF GERMS AND BACTERIA*

NON-SCENTED

50 WIPES

5.5IN X 7IN (14CM X 18CM)

50 PCS NDC: 78198-012-05

LOVE

JUICY

JUICY COUTURE

los angeles, california

HAND SANITIZING WIPES

WORKS IN SECONDS

KILLS 99.9% OF GERMS AND BACTERIA*

NON-SCENTED

50 WIPES

5.5IN X 7IN (14CM X 18CM)

50 PCS NDC: 78198-012-06

JUICY COUTURE

los angeles, california

HAND SANITIZING WIPES

WORKS IN SECONDS

KILLS 99.9% OF GERMS AND BACTERIA*

NON-SCENTED

50 WIPES

5.5IN X 7IN (14CM X 18CM)